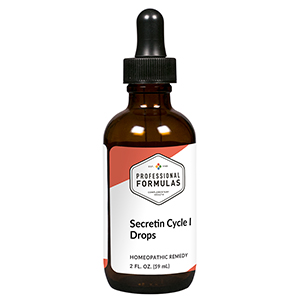 DRUG LABEL: Secretin Cycle I Drops
NDC: 63083-2163 | Form: LIQUID
Manufacturer: Professional Complementary Health Formulas
Category: homeopathic | Type: HUMAN OTC DRUG LABEL
Date: 20190815

ACTIVE INGREDIENTS: SUS SCROFA ADRENAL GLAND 6 [hp_X]/59 mL; BOS TAURUS BRAIN 6 [hp_X]/59 mL; BOS TAURUS HYPOTHALAMUS 6 [hp_X]/59 mL; BOS TAURUS LARGE INTESTINE 6 [hp_X]/59 mL; BEEF KIDNEY 6 [hp_X]/59 mL; BEEF LIVER 6 [hp_X]/59 mL; BOS TAURUS LYMPH VESSEL 6 [hp_X]/59 mL; BOS TAURUS SPLEEN 6 [hp_X]/59 mL; HYSSOPUS OFFICINALIS WHOLE 6 [hp_X]/59 mL; SECRETIN, UNSPECIFIED 9 [hp_X]/59 mL
INACTIVE INGREDIENTS: ALCOHOL; WATER

C163

ACTIVE INGREDIENTS

Adrenal 6X, 9X, 12X
Brain 6X, 9X, 12X
Hypothalamus 6X, 9X, 12X
Intestine 6X, 9X, 12X
Kidney 6X, 9X, 12X
Liver 6X, 9X, 12X
Lymph 6X, 9X, 12X
Spleen 6X, 9X, 12X
Thymus 6X, 9X, 12X
Secretin 9X, 12X, 30X

QUESTIONS

Professional Formulas

PO Box 2034 Lake Oswego, OR 97035

INDICATIONS

For the temporary relief of indigestion or heartburn.*

PURPOSE

*Claims based on traditional homeopathic practice, not accepted medical evidence. Not FDA evaluated.

WARNINGS

In case of overdose, get medical help or contact a poison control center right away.

Keep out of the reach of children.

PREGNANCY OR BREAST FEEDING

If pregnant or breastfeeding, ask a healthcare professional before use.

DIRECTIONS

Place drops under tongue 30 minutes before/after meals. Adults and children 12 years and over: Take 10 drops up to 3 times per day. Consult a physician for use in children under 12 years of age.

OTHER INFORMATION

Tamper resistant. If seal is broken, do not use. After opening, close container tightly and store at room temperature away from heat.

INACTIVE INGREDIENTS

20% ethanol, purified water.

LABEL

Est 1985

Professional Formulas

Complementary Health

Secretin Cycle I Drops

Homeopathic Remedy

2 FL. OZ. (59 mL)